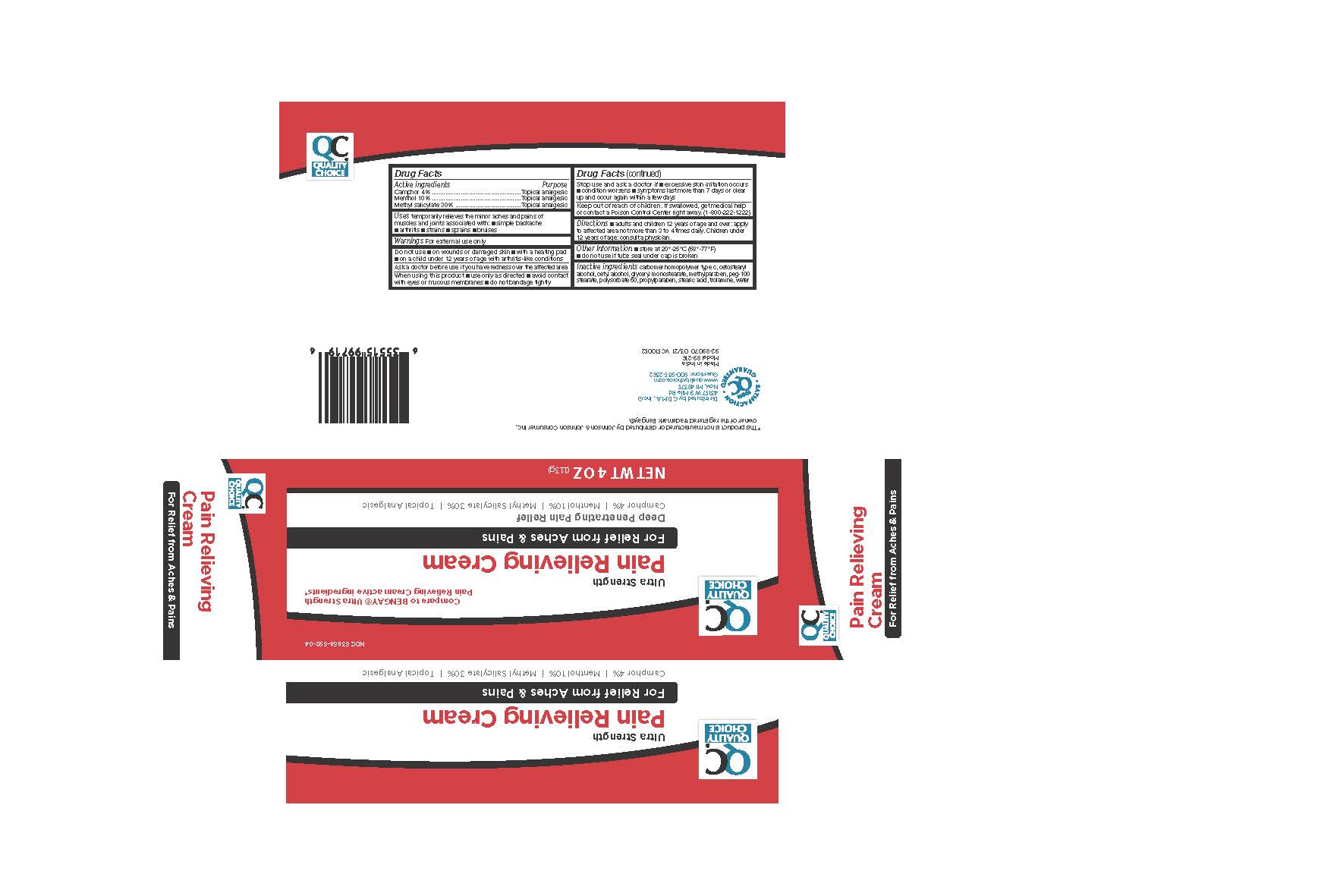 DRUG LABEL: Quality Choice Ultra Strength Pain Relieving Cream
NDC: 63868-692 | Form: CREAM
Manufacturer: QUALITY CHOICE (Chain Drug Marketing Association)
Category: otc | Type: HUMAN OTC DRUG LABEL
Date: 20241218

ACTIVE INGREDIENTS: CAMPHOR (NATURAL) 40 mg/1 g; MENTHOL, UNSPECIFIED FORM 100 mg/1 g; METHYL SALICYLATE 300 mg/1 g
INACTIVE INGREDIENTS: CARBOMER HOMOPOLYMER TYPE C (ALLYL PENTAERYTHRITOL CROSSLINKED); GLYCERYL MONOSTEARATE; CETYL ALCOHOL; CETOSTEARYL ALCOHOL; POLYOXYL 100 STEARATE; POLYSORBATE 60; WATER; METHYLPARABEN; STEARIC ACID; TROLAMINE; PROPYLPARABEN

Quality Choice Ultra Strength Pain Relieving Cream

Active ingredient

Camphor 4%

Menthol 10%

Methyl salicylate 30%

Purpose

Camphor - Topical analgesic

Menthol - Topical analgesic

Methyl salicylate - Topical analgesic

Uses

temporarily relieves minor aches and pains of muscles and joints associated with:

- simple backache
- arthritis
- strains
- sprains
- bruises

Warnings

For external use only

Do not Use

- on wounds or damaged skin
- with a healing pad
- on a child under 12 years of age with arthritis-like conditions

Ask a doctor before use if you have

redness over the affected area

When using this product

- use only as directed
- avoid contact with eyes or mucous membranes
- do not bandage tightly

Stop use and ask a doctor if

- skin redness or excessive irritation of the skin occurs
- condition worsens
- symptoms persist for more than 7 days or clear up and occur again within a few days

Keep Out of Reach of Children

If swallowed, get medical help or contact a Poison Control Center right away (1-800-222-1222)

Directions

- adults and children 12 years and over; apply to affected area not more than 3 to 4 times daily
- children under 12 years of age; consult a physician

Other Information

- Store at 20-25 C (68-77F)
- do not use if tube seal under cap is broken

Inactive Ingredients

carbomer homopolymer type c, cetostearyl alcohol, cetyl alcohol, glyceryl monostearate, methylparaben, peg-100 stearate, polysorbate 60, propylparaben, stearic acid, trolamine, water